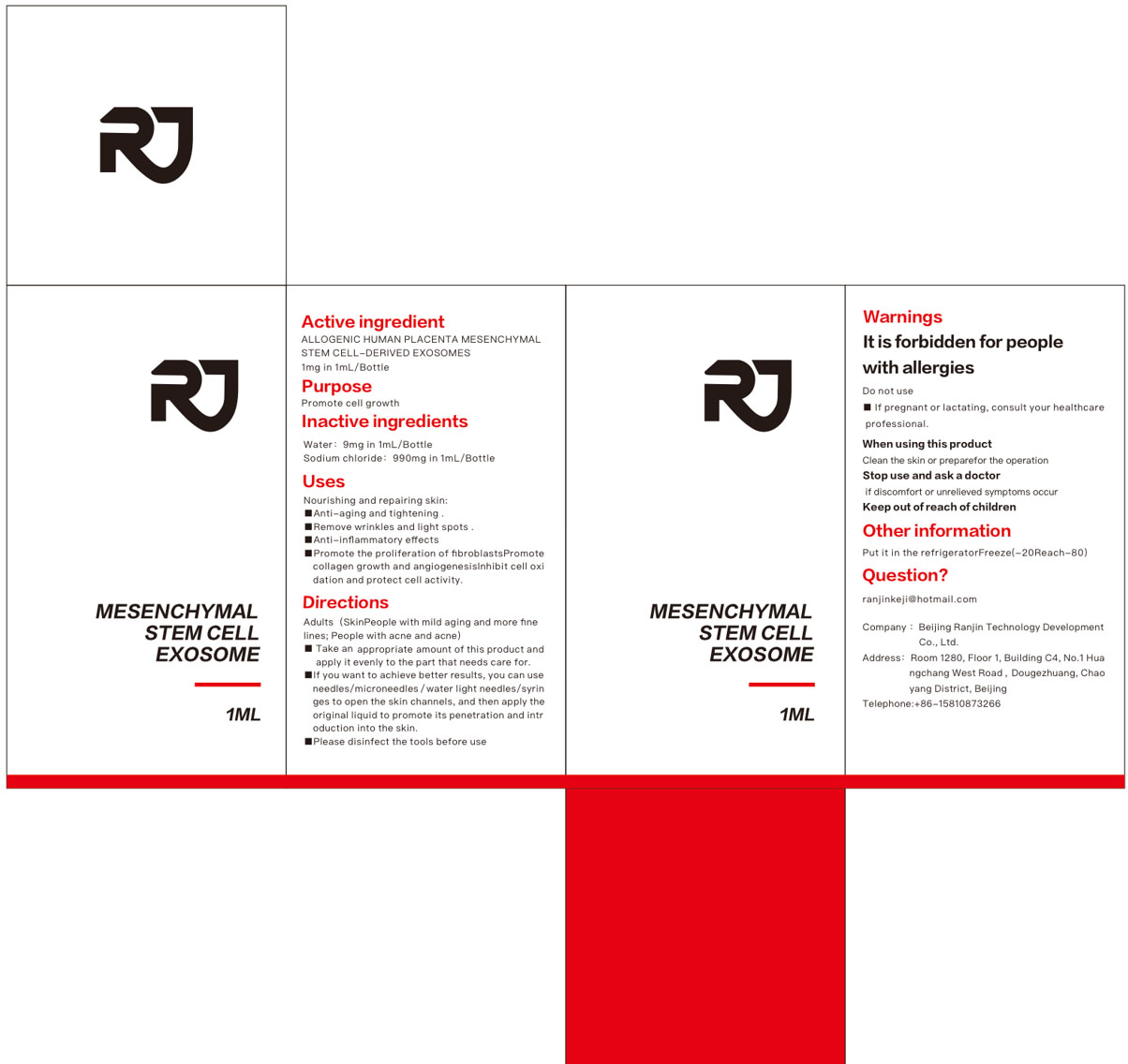 DRUG LABEL: Mesenchymal stem cell exosome solution
NDC: 84553-001 | Form: LIQUID
Manufacturer: Beijing Ranjin Technology Development Co Ltd
Category: otc | Type: HUMAN OTC DRUG LABEL
Date: 20240717

ACTIVE INGREDIENTS: ALLOGENIC HUMAN PLACENTA MESENCHYMAL STEM CELL-DERIVED EXOSOMES 1 g/1 mL
INACTIVE INGREDIENTS: WATER; SODIUM CHLORIDE

84553-001-01

Active ingrredient

Allogenic human placenta mesenchymal srem cell derived exosomes

Purpose

Promote cell growth

Uses

Nourishing and repairing skin:

■Anti-aging and tightening .

■Remove wrinkles and light spots .

■Anti-inflammatory effects

■Promote the proliferation of fibroblastsPromote collagen growth and angiogenesisInhibit cell oxidation and protect cell activity.

Warnings

It is forbidden for people with allergies.

Do not use

If pregnant or lactating, consult your health care professional.

When using this product

Clean the skin or prepare for the operation

Stop use and ask a doctor

If discomfort or unrelieved symptoms occur

Keep out of reach of children

If product is swallowed, get medical help or contact a Poison Control Center right away.

Directions

Adults (SkinPeople with mild aging and more fine lines; People with acne and acne)
■ Take an appropriate amount of this product and apply it evenly to the part that needs care for.
■If you want to achieve better results, you can use needles/microneedles/water light needles/syringes to open the skin channels,
and then apply the original liquid to promote its penetration and introduction into the skin.
■Please disinfect the tools before use.

Other information

Put it in the refrigeratorFreeze (-20Reach-80)

Question?

ranjinkeji@hotmail.com

Inactive ingredient

Sodium chloride, Water

Label

1